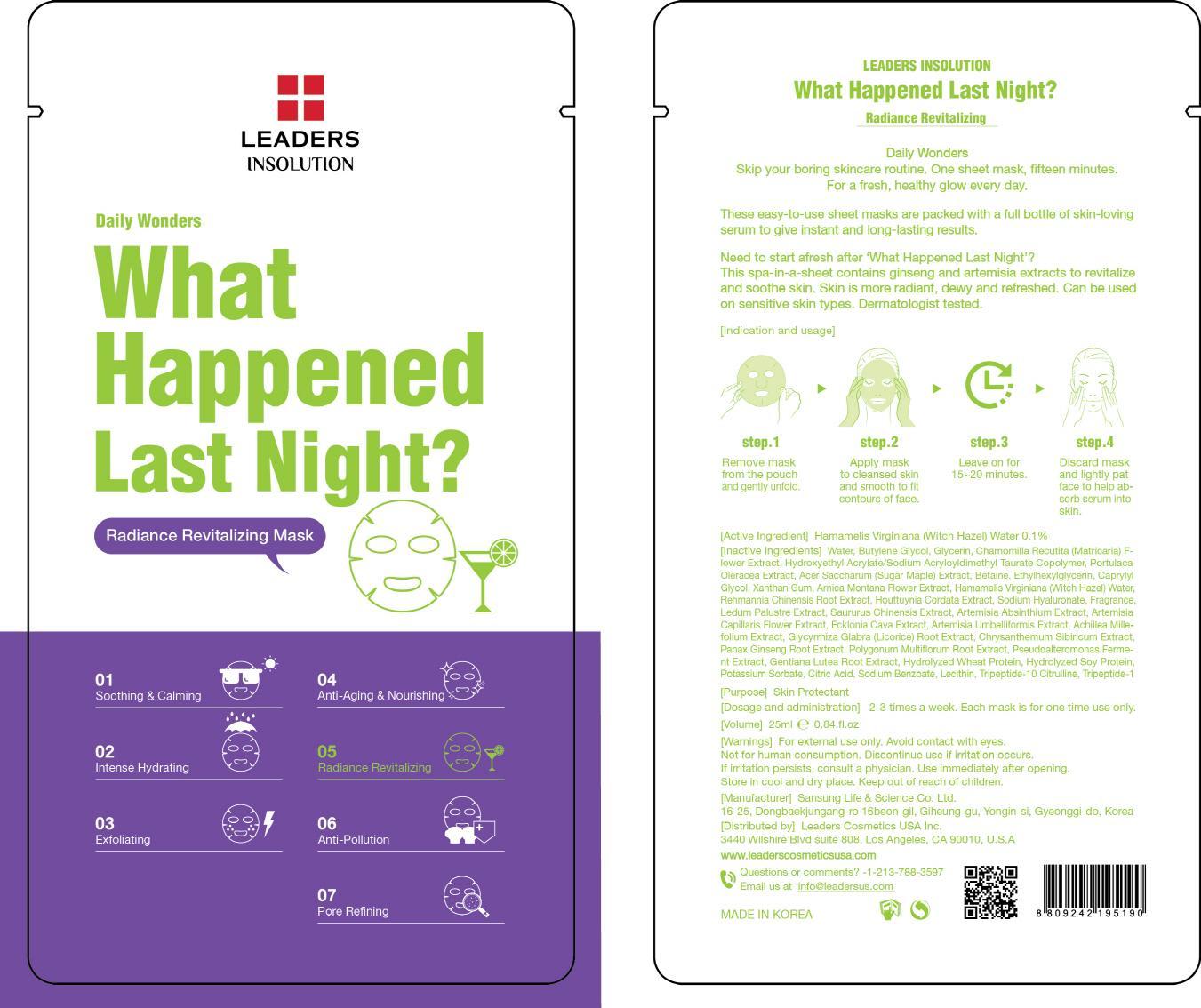 DRUG LABEL: What Happened Last Night
NDC: 69424-340 | Form: PATCH
Manufacturer: SANSUNG LIFE & SCIENCE CO., LTD.
Category: otc | Type: HUMAN OTC DRUG LABEL
Date: 20150529

ACTIVE INGREDIENTS: Witch Hazel 0.025 mg/25 mL
INACTIVE INGREDIENTS: Water; Butylene Glycol

ACTIVE INGREDIENT

Active Ingredient: Hamamelis Virginiana (Witch Hazel) Water 0.1%

INACTIVE INGREDIENT

Inactive Ingredients: Water, Butylene Glycol, Glycerin, Chamomilla Recutita (Matricaria) Flower Extract, Hydroxyethyl Acrylate/Sodium Acryloyldimethyl Taurate Copolymer, Portulaca Oleracea Extract, Acer Saccharum (Sugar Maple) Extract, Betaine, Ethylhexylglycerin, Caprylyl Glycol, Xanthan Gum, Arnica Montana Flower Extract, Rehmannia Chinensis Root Extract, Houttuynia Cordata Extract, Sodium Hyaluronate, Fragrance, Ledum Palustre Extract, Saururus Chinensis Extract, Artemisia Absinthium Extract, Artemisia Capillaris Flower Extract, Ecklonia Cava Extract, Artemisia Umbelliformis Extract, Achillea Millefolium Extract, Glycyrrhiza Glabra (Licorice) Root Extract, Chrysanthemum Sibiricum Extract, Panax Ginseng Root Extract, Polygonum Multiflorum Root Extract, Pseudoalteromonas Ferment Extract, Gentiana Lutea Root Extract, Hydrolyzed Wheat Protein, Hydrolyzed Soy Protein, Potassium Sorbate, Citric Acid, Sodium Benzoate, Lecithin, Tripeptide-10 Citrulline, Tripeptide-1

PURPOSE

Purpose: Skin Protectant

WARNINGS

Warnings: For external use only. Avoid contact with eyes. Not for human consumption. Discontinue use if irritation occurs. If irritation persists, consult a physician. Use immediately after opening. Store in cool and dry place. Keep out of reach of children.

KEEP OUT OF REACH OF CHILDREN

INDICATIONS & USAGE

Indication and usage: Step 1. Remove mask from the pouch and gently unfold. Step 2. Apply mask to cleansed skin and smooth to fit contours of face. Step 3. Leave on for 10~15 minutes. Step 4. Discard mask and lightly pat face to help absorb serum into skin.

DOSAGE & ADMINISTRATION

Dosage and administration: 2-3 times a week. Each mask is for one time use only.